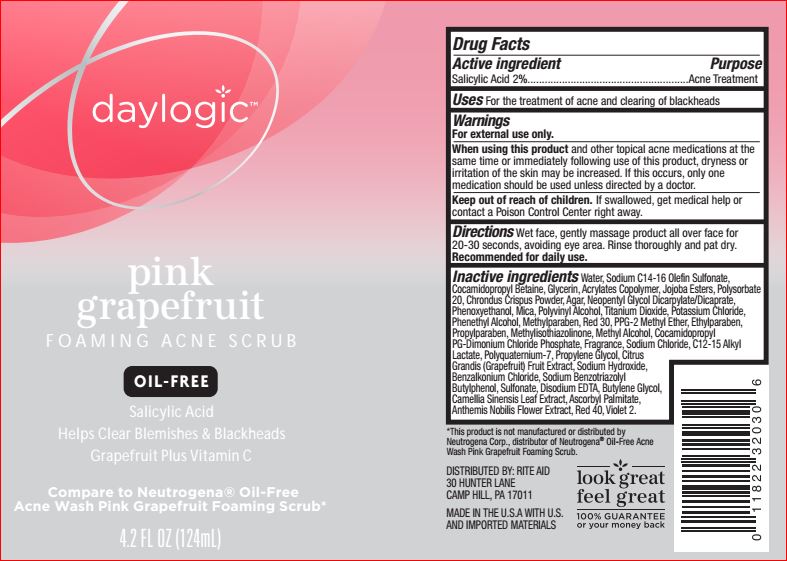 DRUG LABEL: Pink Grapefruit Foaming Acne Scrub
NDC: 11822-1227 | Form: GEL
Manufacturer: Rite Aid
Category: otc | Type: HUMAN OTC DRUG LABEL
Date: 20180613

ACTIVE INGREDIENTS: Salicylic Acid 2 g/100 mL
INACTIVE INGREDIENTS: Water; Sodium C14-16 Olefin Sulfonate; Cocamidopropyl Betaine; Glycerin; Polysorbate 20; CHONDRUS CRISPUS; Agar; NEOPENTYL GLYCOL DICAPRYLATE/DICAPRATE; Phenoxyethanol; Mica; POLYVINYL ALCOHOL, UNSPECIFIED; Titanium Dioxide; Potassium Chloride; PHENYLETHYL ALCOHOL; Methylparaben; D&C RED NO. 30; PPG-2 Methyl Ether; Ethylparaben; Propylparaben; Methylisothiazolinone; Methyl Alcohol; Cocamidopropyl PG-Dimonium Chloride Phosphate; Sodium Chloride; C12-15 Alkyl Lactate; Propylene Glycol; PUMMELO; Sodium Hydroxide; Benzalkonium Chloride; Sodium Benzotriazolyl Butylphenol Sulfonate; EDETATE DISODIUM; Butylene Glycol; GREEN TEA LEAF; Ascorbyl Palmitate; CHAMAEMELUM NOBILE FLOWER; FD&C RED NO. 40; D&C VIOLET NO. 2

Drug Facts

Active ingredient Purpose

Salicylic Acid 2%.....................Acne Treatment

INDICATIONS AND USAGE

Uses For the treatment of acne and clearing of blackheads

Warnings
For external use only.
When using this product and other topical acne medications at the
same time or immediately following use of this product, dryness or
irritation of the skin may be increased. If this occurs, only one
medication should be used unless directed by a doctor.

Keep out of reach of children. If swallowed, get medical help or
contact a Poison Control Center right away

DOSAGE AND ADMINISTRATION

Directions Wet face, gently massage product all over face for
20-30 seconds, avoiding eye area. Rinse thoroughly and pat dry.
Recommended for daily use.

Inactive ingredients

Water
Sodium C14-16 Olefin Sulfonate
Cocamidopropyl Betaine
Glycerin
Acrylates Copolymer
Jojoba Esters
Polysorbate 20
Chrondus Crispus Powder
Agar
Neopentyl Glycol Dicarpylate/Dicaprate
Phenoxyethanol
Mica
Polyvinyl Alcohol
Titanium Dioxide
Potassium Chloride
Phenethyl Alcohol
Methylparaben
Red 30
PPG-2 Methyl Ether
Ethylparaben
Propylparaben
Methylisothiazolinone
Methyl Alcohol
Cocamidopropyl PG-Dimonium Chloride Phosphate
Fragrance
Sodium Chloride
C12-15 Alkyl Lactate
Polyquaternium-7
Propylene Glycol
Citrus Grandis (Grapefruit) Fruit Extract
Sodium Hydroxide

Benzalkonium Chloride
Sodium Benzotriazolyl Butylphenol Sulfonate
Disodium EDTA
Butylene Glycol
Camellia Sinensis Leaf Extract
Ascorbyl Palmitate
Anthemis Nobilis Flower Extract
Red 40
Violet 2